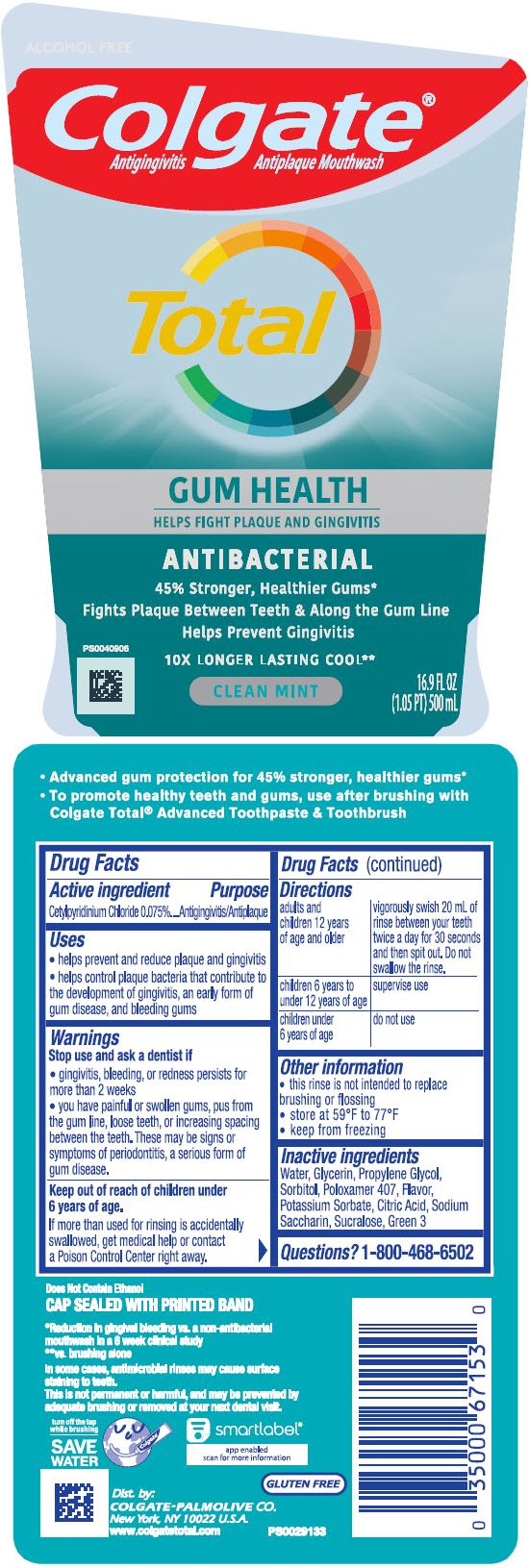 DRUG LABEL: Colgate Total Advanced Gum Health Mouthwash
NDC: 35000-723 | Form: RINSE
Manufacturer: Colgate-Palmolive Company
Category: otc | Type: HUMAN OTC DRUG LABEL
Date: 20241001

ACTIVE INGREDIENTS: CETYLPYRIDINIUM CHLORIDE 0.75 mg/1 mL
INACTIVE INGREDIENTS: WATER; GLYCERIN; PROPYLENE GLYCOL; SORBITOL; POTASSIUM SORBATE; ANHYDROUS CITRIC ACID; SACCHARIN SODIUM; SUCRALOSE; POLOXAMER 407; FD&C GREEN NO. 3

Colgate® Total® Advanced Gum Health Mouthwash

Drug Facts

Active ingredient

Cetylpyridinium chloride 0.075%

Purpose

Antigingivitis/Antiplaque

Uses

- helps prevent and reduce plaque and gingivitis
- helps control plaque bacteria that contribute to the development of gingivitis, an early form of gum disease, and bleeding gums

Warnings

Stop use and ask a dentist if

- gingivitis, bleeding, or redness persists for more than 2 weeks
- you have painful or swollen gums, pus from the gum line, loose teeth, or increasing spacing between the teeth. These may be signs or symptoms of periodontitis, a serious form of gum disease.

Keep out of reach of children under 6 years of age.

If more than used for rinsing is accidentally swallowed, get medical help or contact a Poison Control center right away.

Directions

adults and children 12 years of age and older | vigorously swish 20 mL of rinse between your teeth twice a day for 30 seconds and then spit out. Do not swallow the rinse.
children 6 years to under 12 years of age | supervise use
children under 6 years of age | do not use

Other information

- this rinse is not intended to replace brushing or flossing
- store at 59°F to 77°F
- keep from freezing

Inactive ingredients

water, glycerin, propylene glycol, sorbitol, poloxamer 407, flavor, potassium sorbate, citric acid, sodium saccharin, sucralose, FD&C green no. 3

Questions?

1-800-468-6502

Dist. by:
COLGATE-PALMOLIVE CO.
New York, NY 10022 U.S.A.

PRINCIPAL DISPLAY PANEL - 500 mL Bottle Label

Colgate®
Antigingivitis Antiplaque Mouthwash

Total

GUM HEALTH
HELPS FIGHT PLAQUE AND GINGIVITIS

ANTIBACTERIAL
45% Stronger, Healthier Gums*

Fights Plaque Between Teeth & Along the Gum Line

Helps Prevent Gingivitis

10X LONGER LASTING COOL**

CLEAN MINT

16.9 FL OZ
(1.05 PT) 500 mL

P80040906